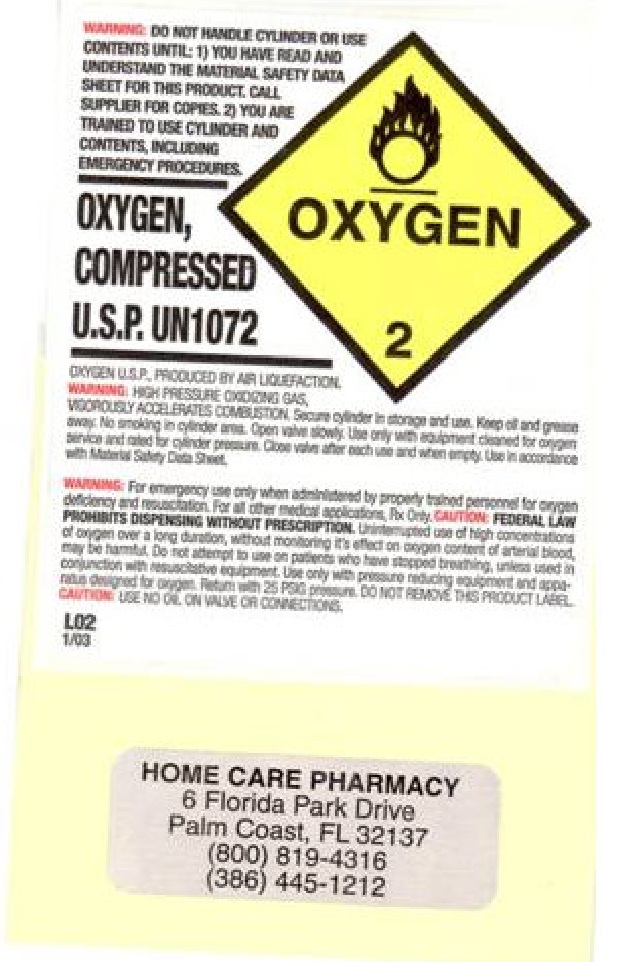 DRUG LABEL: Oxygen, Compressed
NDC: 23644-001 | Form: GAS
Manufacturer: Home Care Pharmacy of Palm Coast, Inc.
Category: prescription | Type: HUMAN PRESCRIPTION DRUG LABEL
Date: 20111221

ACTIVE INGREDIENTS: OXYGEN 1 L/1 L

OXYGEN, COMPRESSED

Packaging

WARNING: DO NOT HANDLE CYLINDER OR USE CONTENTS UNTIL: 20 YOU HAVE READ AND UNDERSTAND THE TMATERIAL SAFETY DATA SHEET FOR THIS PRODUCT. CALL SUPPLIER FOR COPIES. 20 YOU ARE TRAINED TO USE CYLINDER AND CONTENTS INCLUDING EMERGENCY PROCEDURES.

---

OXYGEN, COMPRESSED U.S.P. UN1072

-----

OXYGEN U.S.P., PRODUCED BY AIR LIQUEFACTION

WARNING: HIGH PRESSURE OXIDIZING GAS, VIGOROUSLY ACCELERATES COMBUSTION. Secure cylinder to storage and use. Keep oil and grease away. No smoking in cylinder area. Open valve slowly. Use only with equipment designed for oxygen device and rated for cylender pressure. Close valve after each use and when empty. Use i accordance with Material Safety Data Sheet.

WARNING: For emergency use only when administered by properly trained personnel for oxygen deficiency and resuscitation. For all other medical applications, Rx Only. CAUTION: FEDERAL, LAW PROHIBITS DISPENSING WITHOUT PRESCRIPTION.. Uninterrupted use of hgh concentrations of oxygen over a long duration without monitoring its effect on oxygen content of arterial blood may be harmful. Do not attempt to use on patients who have stopped breathing, unless used in conjunction with resuscitative equipment. Use only with pressure reducing equipment and apparatus designed for oxygen. Returns with 25PSG pressure. DO NOT REMOVE THIS PRODUCT LABEL.

CAUTION: USE NO OIL ON VALVE OR CONNECTIONS.